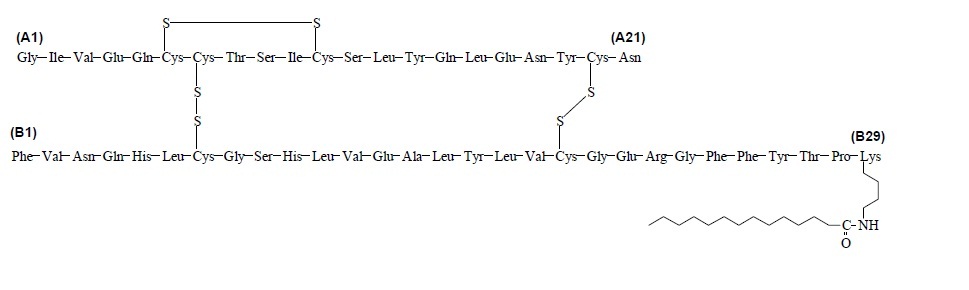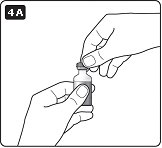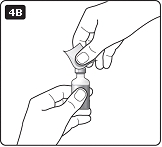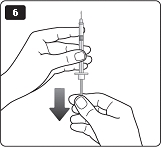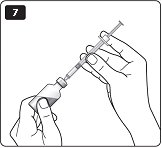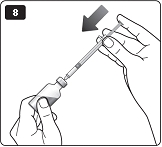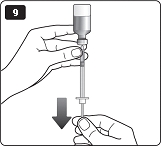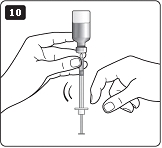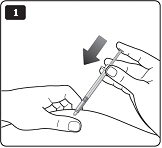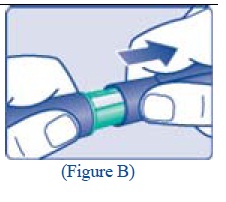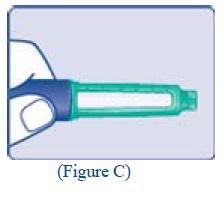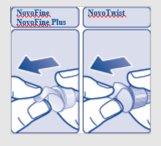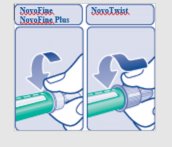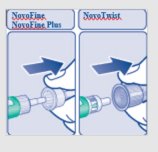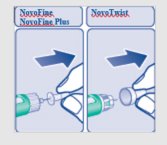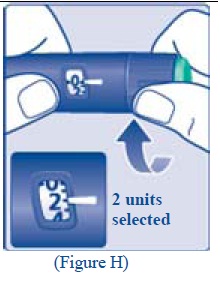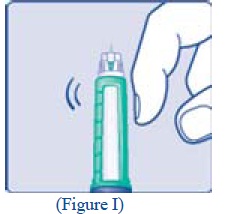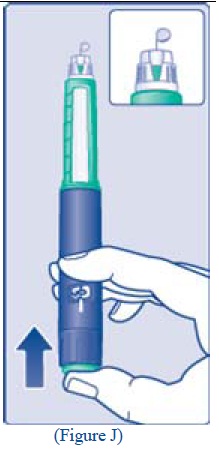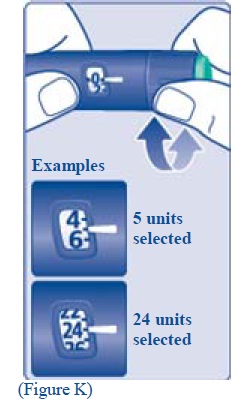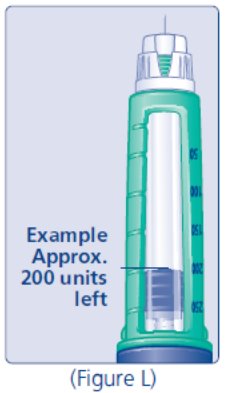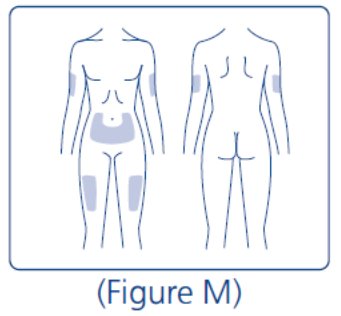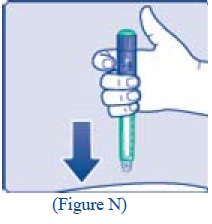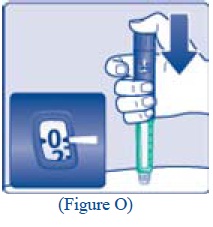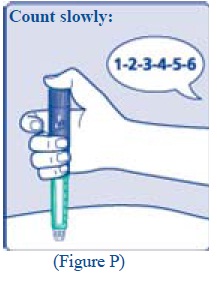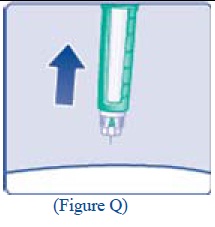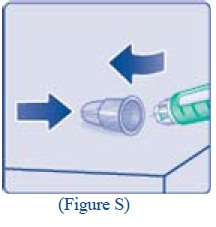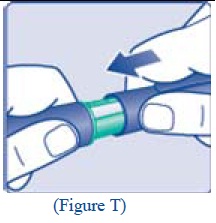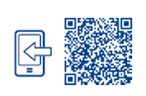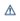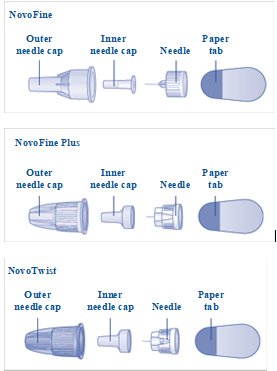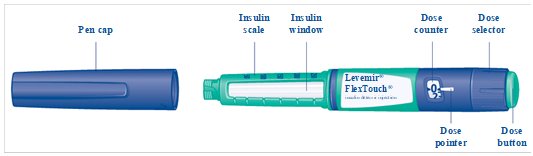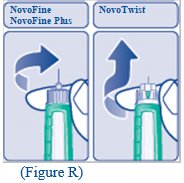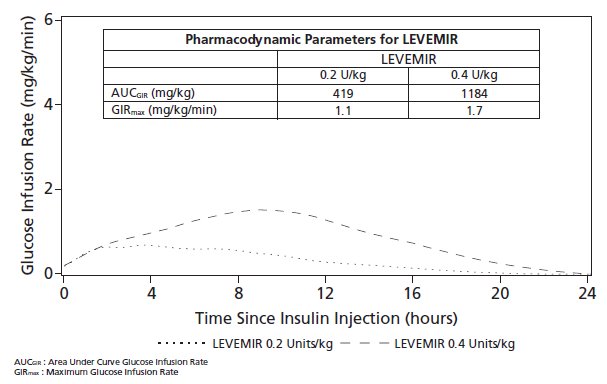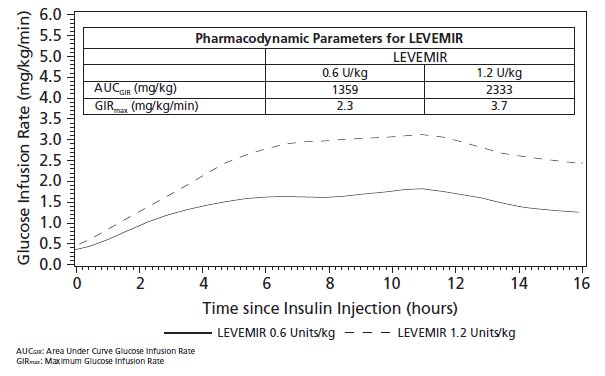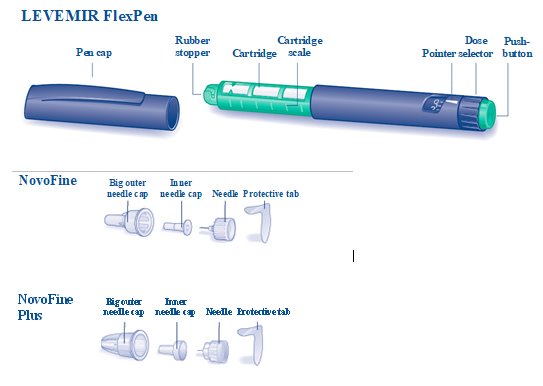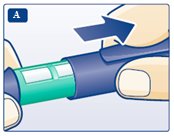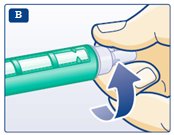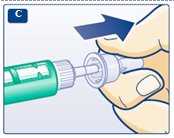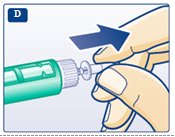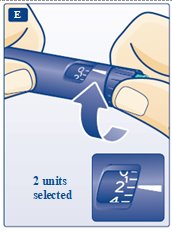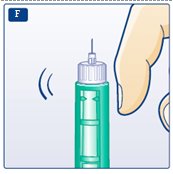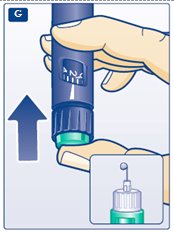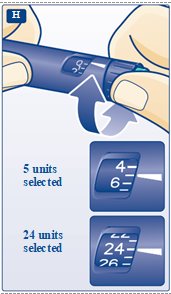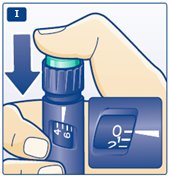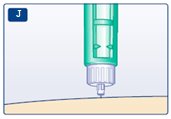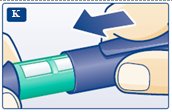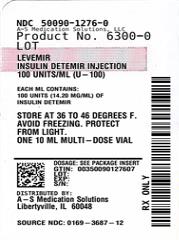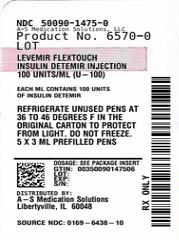 DRUG LABEL: Levemir
NDC: 50090-1276 | Form: INJECTION, SOLUTION
Manufacturer: A-S Medication Solutions
Category: prescription | Type: HUMAN PRESCRIPTION DRUG LABEL
Date: 20241009

ACTIVE INGREDIENTS: INSULIN DETEMIR 100 [iU]/1 mL
INACTIVE INGREDIENTS: SODIUM PHOSPHATE, DIBASIC, UNSPECIFIED FORM; GLYCERIN; METACRESOL; PHENOL; SODIUM CHLORIDE; ZINC; WATER; HYDROCHLORIC ACID; SODIUM HYDROXIDE

HIGHLIGHTS OF PRESCRIBING INFORMATION

These highlights do not include all the information needed to use LEVEMIR® safely and effectively.
See full prescribing information for LEVEMIR.
LEVEMIR® (insulin detemir) injection, for subcutaneous use
Initial U.S. Approval: 2005

1 INDICATIONS AND USAGE

LEVEMIR is a long-acting human insulin analog indicated to improve glycemic control in adult and pediatric patients with diabetes mellitus (1).

Limitations of Use:

Not recommended for the treatment of diabetic ketoacidosis.

2 DOSAGE AND ADMINISTRATION

- See Full Prescribing Information for important administration instructions (2.1).
- Inject subcutaneously into the thigh, upper arm, or abdomen (2.1).
- Rotate injection sites to reduce risk of lipodystrophy and localized cutaneous amyloidosis (2.1).
- Individualize and titrate the dose of LEVEMIR based on the patient’s metabolic needs, blood glucose monitoring results, and glycemic control goal (2.2).
- Administer subcutaneously once daily or in divided doses twice daily (2.2).
- See Full Prescribing Information for recommended starting dose in insulin naïve patients and patients already on insulin therapy (2.3, 2.4).

3 DOSAGE FORMS AND STRENGTHS

Injection: 100 units/mL (U-100) of insulin detemir available as:

- 3 mL single-patient-use FlexPen® prefilled pen (3)
- 10 mL multiple-dose vial (3)

4 CONTRAINDICATIONS

- During episodes of hypoglycemia (4)
- Hypersensitivity to insulin detemir or any of the excipients in LEVEMIR (4)

5 WARNINGS AND PRECAUTIONS

- Never Share a LEVEMIR FlexPen, insulin syringe, or needle between patients, even if the needle is changed (5.1).
- Hyperglycemia or hypoglycemia with changes in insulin regimen: Make changes to a patient’s insulin regimen (e.g., insulin strength, manufacturer, type, injection site or method of administration) under close medical supervision with increased frequency of blood glucose monitoring (5.2).
- Hypoglycemia: May be life-threatening. Increase frequency of glucose monitoring with changes to: insulin dosage, concomitant drugs, meal pattern, physical activity; and in patients with renal impairment or hepatic impairment or hypoglycemia unawareness (5.3).
- Hypoglycemia due to medication errors: Accidental mix-ups between insulin products can occur. Instruct patients to check insulin labels before injection (5.4).
- Hypersensitivity reactions: Severe, life-threatening, generalized allergy, including anaphylaxis, can occur. Discontinue LEVEMIR, monitor and treat if indicated (5.5).
- Hypokalemia: May be life-threatening. Monitor potassium levels in patients at risk for hypokalemia and treat if indicated (5.6).
- Fluid retention and heart failure with concomitant use of thiazolidinediones (TZDs): Observe for signs and symptoms of heart failure; consider dosage reduction or discontinuation if heart failure occurs (5.7).

6 ADVERSE REACTIONS

Adverse reactions associated with LEVEMIR include hypoglycemia, allergic reactions, injection site reactions, lipodystrophy, rash and pruritus (6).

To report SUSPECTED ADVERSE REACTIONS, contact Novo Nordisk Inc. at 1-800-727-6500 or FDA at 1-800-FDA-1088 or www.fda.gov/medwatch

7 DRUG INTERACTIONS

- Drugs that Affect Glucose Metabolism: Adjustment of insulin dosage may be needed. (7)
- Antiadrenergic Drugs (e.g., beta-blockers, clonidine, guanethidine, and reserpine): Signs and symptoms of hypoglycemia may be reduced or absent. (5.3, 7)

FULL PRESCRIBING INFORMATION

1 INDICATIONS AND USAGE

LEVEMIR is indicated to improve glycemic control in adult and pediatric patients with diabetes mellitus.

Limitations of Use

LEVEMIR is not recommended for the treatment of diabetic ketoacidosis.

2 DOSAGE AND ADMINISTRATION

2.1 Important Administration Instructions

- Always check insulin labels before administration [see Warnings and Precautions (5.4)].
- Visually inspect for particulate matter and discoloration. Only use LEVEMIR if the solution appears clear and colorless.
- Inject LEVEMIR subcutaneously into the thigh, upper arm, or abdomen.
- Rotate injection sites within the same region from one injection to the next to reduce the risk of lipodystrophy and localized cutaneous amyloidosis. Do not inject into areas of lipodystrophy or localized cutaneous amyloidosis [see Warnings and Precautions (5.2), Adverse Reactions (6)].
- During changes to a patient’s insulin regimen, increase the frequency of blood glucose monitoring [see Warnings and Precautions (5.2)].
- Do not dilute or mix LEVEMIR with any other insulin or solution.
- Do not administer LEVEMIR intravenously or in an insulin infusion pump.
- LEVEMIR FlexPen dials in 1-unit increments.
- Use the LEVEMIR FlexPen with caution in patients with visual impairment who may rely on audible clicks to dial their dose.

2.2 General Dosing Instructions

- LEVEMIR can be administered by subcutaneous injection once or twice daily. Administer once daily doses with the evening meal or at bedtime. For twice daily dosing, administer the evening dose with the evening meal, at bedtime, or 12 hours after the morning dose.
- Individualize and titrate the dose of LEVEMIR based on the patient’s metabolic needs, blood glucose monitoring results, and glycemic control goal.
- Dose adjustments may be needed with changes in physical activity, changes in meal patterns (i.e., macronutrient content or timing of food intake), changes in renal or hepatic function or during acute illness to minimize the risk of hypoglycemia or hyperglycemia [see Warnings and Precautions (5.3)].
- In patients with type 1 diabetes, LEVEMIR must be used in a regimen with rapid-acting or short-acting insulin.

2.3 Starting Dose in Insulin Naïve Patients

Recommended Starting Dosage in Patients with Type 1 Diabetes

The recommended starting dose of LEVEMIR in patients with type 1 diabetes mellitus is approximately one-third to one-half of the total daily insulin dose. The remainder of the total daily insulin dose should be administered as short-acting pre-meal insulin. As a general rule, 0.2 to 0.4 units of insulin per kilogram of body weight can be used to calculate the initial total daily insulin dose in insulin naïve patients with type 1 diabetes.

Recommended Starting Dosage in Patients with Type 2 Diabetes

The recommended starting dose of LEVEMIR in patients with type 2 diabetes mellitus inadequately controlled on oral antidiabetic medications or a GLP-1 receptor agonist is 10 units (or 0.1 units/kg to 0.2 units/kg) given once daily in the evening or divided into a twice daily regimen.

2.4 Switching to LEVEMIR from Other Insulin Therapies

Dosage adjustments are recommended to lower the risk of hypoglycemia when switching patients to LEVEMIR from another insulin therapy [see Warnings and Precautions (5.3)].

- If converting from insulin glargine to LEVEMIR, the change can be done on a unit-to-unit basis.
- If converting from NPH insulin, the change can be done on a unit-to-unit basis. However, some patients with type 2 diabetes mellitus may require more LEVEMIR than NPH insulin, as observed in one trial [see Clinical Studies (14)].

3 DOSAGE FORMS AND STRENGTHS

Injection: 100 units/mL (U-100), is a clear, colorless, solution available as:

- 3 mL single-patient-use FlexPen prefilled pen
- 10 mL multiple-dose vial

4 CONTRAINDICATIONS

LEVEMIR is contraindicated:

- During episodes of hypoglycemia [see Warnings and Precautions (5.3)]
- In patients with hypersensitivity to insulin detemir or any of the excipients in LEVEMIR. Reactions have included anaphylaxis [see Warnings and Precautions (5.5) and Adverse Reactions (6.1)].

5 WARNINGS AND PRECAUTIONS

5.1 Never Share a LEVEMIR FlexPen, Needle, or Insulin Syringe between Patients

LEVEMIR FlexPen prefilled pens must never be shared between patients, even if the needle is changed. Patients using LEVEMIR vials should never share needles or syringes with another person. Sharing poses a risk for transmission of blood-borne pathogens.

5.2 Hyperglycemia or Hypoglycemia with Changes in Insulin Regimen

Changes in an insulin regimen (e.g., insulin strength, manufacturer, type, injection site or method of administration) may affect glycemic control and predispose to hypoglycemia [see Warnings and Precautions (5.4)] or hyperglycemia. Repeated insulin injections into areas of lipodystrophy or localized cutaneous amyloidosis have been reported to result in hyperglycemia; and a sudden change in the injection site (to an unaffected area) has been reported to result in hypoglycemia [see Adverse Reactions (6)].

Make any changes to a patient’s insulin regimen under close medical supervision with increased frequency of blood glucose monitoring. Advise patients who have repeatedly injected into areas of lipodystrophy or localized cutaneous amyloidosis to change the injection site to unaffected areas and closely monitor for hypoglycemia. For patients with type 2 diabetes, dosage adjustments of concomitant antidiabetic products may be needed [see Dosage and Administration (2.4)].

5.3 Hypoglycemia

Hypoglycemia is the most common adverse reaction of insulin, including LEVEMIR [see Adverse Reactions (6.1)]. Severe hypoglycemia can cause seizures, may be life-threatening or cause death. Hypoglycemia can impair concentration ability and reaction time; this may place the patient and others at risk in situations where these abilities are important (e.g., driving or operating other machinery). LEVEMIR, or any insulin, should not be used during episodes of hypoglycemia [see Contraindications (4)].

Hypoglycemia can happen suddenly and symptoms may differ in each patient and change over time in the same patient. Symptomatic awareness of hypoglycemia may be less pronounced in patients with longstanding diabetes, in patients with diabetic neuropathy, using drugs that block the sympathetic nervous system (e.g., beta-blockers) [see Drug Interactions (7)], or who experience recurrent hypoglycemia.

Risk Factors for Hypoglycemia

The risk of hypoglycemia generally increases with intensity of glycemic control. The risk of hypoglycemia after an injection is related to the duration of action of the insulin [see Clinical Pharmacology (12.2)] and, in general, is highest when the glucose lowering effect of the insulin is maximal. As with all insulins, the glucose lowering effect time course of LEVEMIR may vary among different patients or at different times in the same patient and depends on many conditions, including the area of injection as well as the injection site blood supply and temperature.

Other factors which may increase the risk of hypoglycemia include changes in meal pattern (e.g., macronutrient content or timing of meals), changes in level of physical activity, or changes to concomitant drugs [see Drug Interactions (7)]. When a GLP-1 receptor agonist is used in combination with LEVEMIR, the LEVEMIR dose may need to be lowered or more conservatively titrated to minimize the risk of hypoglycemia [see Adverse Reactions (6.1)]. Patients with renal or hepatic impairment may be at higher risk of hypoglycemia [see Use in Specific Populations (8.6, 8.7)].

Risk Mitigation Strategies for Hypoglycemia

Patients and caregivers must be educated to recognize and manage hypoglycemia. Self-monitoring of blood glucose plays an essential role in the prevention and management of hypoglycemia. In patients at higher risk for hypoglycemia and patients who have reduced symptomatic awareness of hypoglycemia, increased frequency of blood glucose monitoring is recommended.

5.4 Hypoglycemia Due to Medication Errors

Accidental mix-ups between insulin products have been reported. To avoid medication errors between LEVEMIR and other insulins, instruct patients to always check the insulin label before each injection.

5.5 Hypersensitivity Reactions

Severe, life-threatening, generalized allergy, including anaphylaxis, can occur with insulins, including LEVEMIR [see Adverse Reactions (6.1)]. If hypersensitivity reactions occur, discontinue LEVEMIR; treat per standard of care and monitor until symptoms and signs resolve. LEVEMIR is contraindicated in patients who have had hypersensitivity reactions to insulin detemir or any of the excipients.

5.6 Hypokalemia

All insulins, including LEVEMIR, cause a shift in potassium from the extracellular to intracellular space, possibly leading to hypokalemia. Untreated hypokalemia may cause respiratory paralysis, ventricular arrhythmia, and death. Monitor potassium levels in patients at risk for hypokalemia if indicated (e.g., patients using potassium-lowering medications, patients taking medications sensitive to serum potassium concentrations).

5.7 Fluid Retention and Heart Failure with Concomitant Use of PPAR-gamma Agonists

Thiazolidinediones (TZDs), which are peroxisome proliferator-activated receptor (PPAR)-gamma agonists, can cause dose-related fluid retention, when used in combination with insulin. Fluid retention may lead to or exacerbate heart failure. Patients treated with insulin, including LEVEMIR, and a PPAR-gamma agonist should be observed for signs and symptoms of heart failure. If heart failure develops, it should be managed according to current standards of care, and discontinuation or dose reduction of the PPAR-gamma agonist must be considered.

6 ADVERSE REACTIONS

The following adverse reactions are discussed elsewhere:

- Hypoglycemia [see Warnings and Precautions (5.3)]
- Hypoglycemia Due to Medication errors [see Warnings and Precautions (5.4)]
- Hypersensitivity Reactions [see Warnings and Precautions (5.5)]
- Hypokalemia [see Warnings and Precautions (5.6)]

6.1 Clinical Trial Experience

Because clinical trials are conducted under widely varying designs, the adverse reaction rates reported in one clinical trial may not be easily compared to those rates reported in another clinical trial, and may not reflect the rates actually observed in clinical practice.

The frequencies of adverse reactions (excluding hypoglycemia) reported during LEVEMIR clinical trials in patients with type 1 diabetes mellitus and type 2 diabetes mellitus are listed in Tables 1-4 below. See Tables 5 and 6 for the hypoglycemia findings.

In two pooled trials, adults with type 1 diabetes were exposed to individualized doses of LEVEMIR (n=767) or NPH (n=388). The mean duration of exposure to LEVEMIR was 153 days, and the total exposure to LEVEMIR was 321 patient-years. The most common adverse reactions are summarized in Table 1.

Table 1: Adverse Reactions Occurring in ≥ 5% of LEVEMIR-Treated Adult Patients with Type 1 Diabetes Mellitus in Two Trials of 16 Weeks and 24 Weeks Duration
 | LEVEMIR, %; (n = 767)
Upper respiratory tract infection | 26.1
Headache | 22.6
Pharyngitis | 9.5
Influenza-like illness | 7.8
Abdominal Pain | 6.0

Adults with type 1 diabetes were exposed to LEVEMIR (n=161) or insulin glargine (n=159). The mean duration of exposure to LEVEMIR was 176 days, and the total exposure to LEVEMIR was 78 patient-years. The most common adverse reactions are summarized in Table 2.

Table 2: Adverse Reactions Occurring in ≥ 5% of LEVEMIR-Treated Adult Patients with Type 1 Diabetes Mellitus in a 26-week Trial
 | LEVEMIR, %; (n = 161)
Upper respiratory tract infection | 26.7
Headache | 14.3
Back pain | 8.1
Influenza-like illness | 6.2
Gastroenteritis | 5.6
Bronchitis | 5.0

In two pooled trials, adults with type 2 diabetes were exposed to LEVEMIR (n=432) or NPH (n=437). The mean duration of exposure to LEVEMIR was 157 days, and the total exposure to LEVEMIR was 186 patient-years. The most common adverse reactions were comparable to that observed in adult patients with type 1 diabetes mellitus; see Table 1.

Pediatric patients with type 1 diabetes were exposed to individualized doses of LEVEMIR (n=232) or NPH (n=115). The mean duration of exposure to LEVEMIR was 180 days, and the total exposure to LEVEMIR was 114 patient-years. The most common adverse reactions are summarized in Table 3.

Table 3: Adverse Reactions Occurring in ≥ 5% of LEVEMIR-Treated Pediatric Patients with Type 1 Diabetes Mellitus in a 26-week Trial
 | LEVEMIR, %; (n = 232)
Upper respiratory tract infection | 35.8
Headache | 31.0
Pharyngitis | 17.2
Gastroenteritis | 16.8
Influenza-like illness | 13.8
Abdominal pain | 13.4
Pyrexia | 10.3
Cough | 8.2
Viral infection | 7.3
Nausea | 6.5
Rhinitis | 6.5
Vomiting | 6.5

Hypoglycemia

Hypoglycemia was the most commonly observed adverse reaction in patients treated with LEVEMIR. The rates of reported hypoglycemia depend on the definition of hypoglycemia used, diabetes type, insulin dose, intensity of glucose control, background therapies, and other intrinsic and extrinsic patient factors. For these reasons, comparing rates of hypoglycemia in clinical trials for LEVEMIR with the incidence of hypoglycemia for other products may be misleading and also, may not be representative of hypoglycemia rates that will occur in clinical practice.

Table 4 (type 1 diabetes) and Table 5 (type 2 diabetes) summarize the incidence of severe and non-severe hypoglycemia in the LEVEMIR clinical trials.

For the adult trials and one of the pediatric trials (Study D), severe hypoglycemia was defined as an event with symptoms consistent with hypoglycemia requiring assistance of another person and associated with either a plasma glucose value below 56 mg/dL (blood glucose below 50 mg/dL) or prompt recovery after oral carbohydrate, intravenous glucose or glucagon administration. For the other pediatric trial (Study I), severe hypoglycemia was defined as an event with semi-consciousness, unconsciousness, coma and/or convulsions in a patient who could not assist in the treatment and who may have required glucagon or intravenous glucose.

For the adult trials and pediatric trial (Study D), non-severe hypoglycemia was defined as an asymptomatic or symptomatic plasma glucose <56 mg/dL (or equivalently blood glucose <50 mg/dL as used in Study A and C) that was self-treated by the patient. For pediatric Study I, non-severe hypoglycemia included asymptomatic events with plasma glucose <65 mg/dL as well as symptomatic events that the patient could self-treat or treat by taking oral therapy provided by the caregiver.

Table 4: Hypoglycemia in Patients with Type 1 Diabetes
 |  | Severe Hypoglycemia |  | Non-Severe Hypoglycemia
 |  | Percent of patients with at least 1 event; (n/total N) | Event/patient/; year | Percent of patients; (n/total N) | Event/patient/; year
Study A; Type 1 Diabetes; Adults; 16 weeks; In combination with; insulin aspart | Twice-Daily; LEVEMIR | 8.7; (24/276) | 0.52 | 88.0; (243/276) | 26.4
Study B; Type 1 Diabetes; Adults; 26 weeks; In combination with; insulin aspart | Twice-Daily; LEVEMIR | 5.0; (8/161) | 0.13 | 82.0; (132/161) | 20.2
Study C; Type 1 Diabetes; Adults; 24 weeks; In combination with; regular insulin | Once-Daily LEVEMIR | 7.5; (37/491) | 0.35 | 88.4; (434/491) | 31.1
Study D; Type 1 Diabetes; Pediatrics; 26 weeks; In combination with; insulin aspart | Once- or Twice Daily LEVEMIR | 15.9; (37/232) | 0.91 | 93.1; (216/232) | 31.6
Study I; Type 1 Diabetes; Pediatrics; 52 weeks; In combination with insulin aspart | Once- or Twice Daily LEVEMIR | 1.7; (3/177) | 0.02 | 94.9; (168/177) | 56.1

Table 5: Hypoglycemia in Patients with Type 2 Diabetes
 |  | Study E; Type 2 Diabetes; Adults; 24 weeks; In combination with; oral agents | Study F; Type 2 Diabetes; Adults; 22 weeks; In combination with; insulin aspart | Study H; Type 2 Diabetes; Adults; 26 weeks in combination with Liraglutide and Metformin
 |  | Twice-Daily LEVEMIR | Once- or Twice Daily LEVEMIR | Once Daily LEVEMIR + Liraglutide +; Metformin
Severe hypoglycemia | Percent of patients with at least 1 event (n/total N) | 0.4; (1/237) | 1.5; (3/195) | 0
Severe hypoglycemia | Event/patient/year | 0.01 | 0.04 | 0
Non-severe hypoglycemia | Percent of patients (n/total N) | 40.5; (96/237) | 32.3; (63/195) | 9.2; (15/163)
Non-severe hypoglycemia | Event/patient/year | 3.5 | 1.6 | 0.29

Hypersensitivity Reactions
Severe, life-threatening, generalized allergy, including anaphylaxis, generalized skin reactions, angioedema, bronchospasm, hypotension, and shock have occurred with insulin, including LEVEMIR, and may be life-threatening.

Insulin Initiation and Intensification of Glucose Control

Intensification or rapid improvement in glucose control has been associated with a transitory, reversible ophthalmologic refraction disorder, worsening of diabetic retinopathy, and acute painful peripheral neuropathy. However, long-term glycemic control decreases the risk of diabetic retinopathy and neuropathy.

Lipodystrophy

Long-term use of insulin, including LEVEMIR, can cause lipodystrophy at the site of repeated insulin injections. Lipodystrophy includes lipohypertrophy (thickening of adipose tissue) and lipoatrophy (thinning of adipose tissue), and may affect insulin absorption [see Dosage and Administration (2.1)].

Weight Gain

Weight gain can occur with insulin therapy, including LEVEMIR, and has been attributed to the anabolic effects of insulin and the decrease in glucosuria [see Clinical Studies (14)]. In the clinical program, the mean change in body weight from baseline in adult patients with type 1 diabetes (Study A, B, and C) treated with LEVEMIR ranged from -0.3 kg to 0.5 kg. The mean change in body weight from baseline in adult patients with type 2 diabetes (Study E, F, and H) treated with LEVEMIR ranged from 0.5 kg to 1.2 kg.

Peripheral Edema

Insulin, including LEVEMIR, may cause sodium retention and edema, particularly if previously poor metabolic control is improved by intensified insulin therapy.

Injection Site Reactions

Patients taking LEVEMIR may experience injection site reactions, including localized erythema, pain, pruritus, urticaria, edema, and inflammation. In clinical studies in adults, three patients treated with LEVEMIR reported injection site pain (0.25%).

Immunogenicity

All insulin products can elicit the formation of insulin antibodies. These insulin antibodies may increase or decrease the efficacy of insulin and may require adjustment of the insulin dose. In clinical trials of LEVEMIR, antibody development has been observed with no apparent impact on glycemic control.

6.2 Postmarketing Experience

The following adverse reactions have been identified during post approval use of LEVEMIR. Because these reactions are reported voluntarily from a population of uncertain size, it is not always possible to reliably estimate their frequency or establish a causal relationship to drug exposure.

Medication errors have been reported in which rapid-acting or short-acting insulins and other insulins, have been accidentally administered instead of LEVEMIR.

Localized cutaneous amyloidosis at the injection site has occurred. Hyperglycemia has been reported with repeated insulin injections into areas of localized cutaneous amyloidosis; hypoglycemia has been reported with a sudden change to an unaffected injection site.

7 DRUG INTERACTIONS

Table 6 includes clinically significant drug interactions with LEVEMIR.

Table 6: Clinically Significant Drug Interactions with LEVEMIR

Drugs That May Increase the Risk of Hypoglycemia
Drugs: |  | Antidiabetic agents, ACE inhibitors, angiotensin II receptor blocking agents, disopyramide, fibrates, fluoxetine, monoamine oxidase inhibitors, pentoxifylline, pramlintide, salicylates, somatostatin analogs (e.g., octreotide), and sulfonamide antibiotics, GLP-1 receptor agonists, DPP-4 inhibitors, SGLT-2 inhibitors.
Intervention: |  | Dosage reductions and increased frequency of glucose monitoring may be required when LEVEMIR is co-administered with these drugs.
Drugs That May Decrease the Blood Glucose Lowering Effect of LEVEMIR
Drugs: |  | Atypical antipsychotics (e.g., olanzapine and clozapine), corticosteroids, danazol, diuretics, estrogens, glucagon, isoniazid, niacin, oral contraceptives, phenothiazines, progestogens (e.g., in oral contraceptives), protease inhibitors, somatropin, sympathomimetic agents (e.g., albuterol, epinephrine, terbutaline), and thyroid hormones.
Intervention: |  | Dosage increases and increased frequency of glucose monitoring may be required when LEVEMIR is co-administered with these drugs.
Drugs That May Increase or Decrease the Blood Glucose Lowering Effect of LEVEMIR
Drugs: |  | Alcohol, beta-blockers, clonidine, and lithium salts. Pentamidine may cause hypoglycemia, which may sometimes be followed by hyperglycemia.
Intervention: |  | Dosage adjustment and increased frequency of glucose monitoring may be required when LEVEMIR is co-administered with these drugs.
Drugs That May Blunt Signs and Symptoms of Hypoglycemia
Drugs: | Beta-blockers, clonidine, guanethidine, and reserpine
Intervention: | Increased frequency of glucose monitoring may be required when LEVEMIR is co-administered with these drugs.

8 USE IN SPECIFIC POPULATIONS

8.1 Pregnancy

Risk Summary

Available data from published studies and postmarketing case reports with LEVEMIR use in pregnant women have not identified a drug-associated risk of major birth defects, miscarriage, or adverse maternal or fetal outcomes. In a randomized, parallel-group, open-label clinical trial that included 152 pregnant women with type 1 diabetes who were administered LEVEMIR once or twice daily, beginning in gestational weeks 8 to 12 or prior to conception, no clear evidence of maternal or fetal risk associated with LEVEMIR was observed (see Data). There are risks to the mother and fetus associated with poorly controlled diabetes in pregnancy (see Clinical Considerations).

Animal reproduction studies were conducted in non-diabetic pregnant rats and rabbits with insulin detemir administration at 3 and 135 times the human dose of 0.5 units/kg/day, respectively, throughout pregnancy. Overall, the effects of insulin detemir did not generally differ from those observed with regular human insulin (see Data).

In the U.S. general population, the estimated background risk of major birth defects and miscarriage in clinically recognized pregnancies is 2 to 4% and 15 to 20%, respectively. The estimated background risk of major birth defects is 6 to 10% in women with pre-gestational diabetes with a peri-conceptional HbA1c >7 and has been reported to be as high as 20 to 25% in women with a peri-conceptional HbA1c >10. The estimated background risk of miscarriage for the indicated population is unknown.

Clinical Considerations

Disease-Associated Maternal and/or Embryo/Fetal Risk

Hypoglycemia and hyperglycemia occur more frequently during pregnancy in patients with pre-gestational diabetes. Poorly controlled diabetes in pregnancy increases the maternal risk for diabetic ketoacidosis, preeclampsia, spontaneous abortions, preterm delivery, and delivery complications. Poorly controlled diabetes increases the fetal risk for major birth defects, stillbirth, and macrosomia-related morbidity.

Data

Human Data

In an open-label clinical trial, pregnant females with type 1 diabetes (n=310) were treated with LEVEMIR (once or twice daily) or NPH insulin (once, twice, or thrice daily); both groups also received preprandial insulin aspart. Approximately half of the study participants in each arm were randomized as pregnant and were exposed to NPH or to other insulins prior to conception and in the first 8 weeks of gestation. The rates of preeclampsia observed in the study were within expected rates for pregnancy complicated by diabetes. No differences in pregnancy outcomes or the health of the fetus and newborn were seen between the two groups. In this study, the proportion of subjects with severe hypoglycemia and non-severe hypoglycemia was similar between the two treatment arms; for the definitions of severe hypoglycemia and non-severe hypoglycemia [see Adverse Reactions (6.1)].

In about a quarter of infants, LEVEMIR was detected in the infant cord blood at levels above the lower level of quantification (<25 pmol/L).

Animal Data

In a fertility and embryonic development study, insulin detemir was administered to female rats before mating, during mating, and throughout pregnancy at doses up to 300 nmol/kg/day (3 times a human dose of 0.5 units/kg/day, based on plasma area under the curve (AUC) ratio). Doses of 150 and 300 nmol/kg/day produced numbers of litters with visceral anomalies. Doses up to 900 nmol/kg/day (approximately 135 times a human dose of 0.5 units/kg/day based on AUC ratio) were given to rabbits during organogenesis. Drug and dose related increases in the incidence of fetuses with gallbladder abnormalities such as small, bilobed, bifurcated, and missing gallbladders were observed at a dose of 900 nmol/kg/day. The rat and rabbit embryo-fetal development studies that included concurrent human insulin control groups indicated that insulin detemir and human insulin had similar effects regarding embryotoxicity and teratogenicity suggesting that the effects seen were the result of hypoglycemia resulting from insulin exposure in normal animals.

8.2 Lactation

Risk Summary

Available data from published literature demonstrate that exogenous human insulin products, including biosynthetic insulins such as insulin detemir, are transferred into human milk. There are no published reports of adverse reactions, including hypoglycemia, in breastfed infants exposed to exogenous human insulin products, including insulin detemir, in breastmilk. There are no data on the effects of exogenous human insulin products, including insulin detemir, on milk production. The developmental and health benefits of breastfeeding should be considered along with the mother’s clinical need for LEVEMIR and any potential adverse effects on the breastfed infant from LEVEMIR or from the underlying maternal condition.

8.4 Pediatric Use

The safety and effectiveness of LEVEMIR to improve glycemic control in pediatric patients with diabetes mellitus have been established. The use of LEVEMIR for this indication is supported by evidence from adequate and well-controlled trials (Studies D and I) in 694 pediatric patients aged 2 to 17 years with type 1 diabetes mellitus [see Clinical Studies (14.2)] and from other studies in pediatric patients and adults with diabetes mellitus [see Clinical Pharmacology (12.3), Clinical Studies (14.3)].

8.5 Geriatric Use

In clinical trials of LEVEMIR, 64 of 1624 patients (4%) in the type 1 diabetes trials and 309 of 1082 patients (29%) in the type 2 diabetes trials were 65 years or older. A total of 52 (7 type 1 and 45 type 2) patients (2%) were 75 years or older. No overall differences in safety or effectiveness were observed between these patients and younger patients, but small sample sizes limits conclusions. Greater sensitivity of some older individuals cannot be ruled out. In geriatric patients, the initial dosing, dosage increments, and maintenance dosage should be conservative to avoid hypoglycemia. Hypoglycemia may be difficult to recognize in the geriatric patients.

8.6 Renal Impairment

No difference was observed in the pharmacokinetics of LEVEMIR between non-diabetic patients with kidney impairment and healthy volunteers. However, some studies with human insulin have shown increased circulating insulin concentrations in patients with kidney impairment. Careful glucose monitoring and dose adjustments of LEVEMIR, may be necessary in patients with kidney impairment [see Clinical Pharmacology (12.3)].

8.7 Hepatic Impairment

Non-diabetic patients with severe hepatic impairment had lower systemic exposures to insulin detemir compared to healthy volunteers. However, some studies with human insulin have shown increased circulating insulin concentrations in patients with liver impairment. Careful glucose monitoring and dosage adjustments of LEVEMIR, may be necessary in patients with hepatic impairment [see Clinical Pharmacology (12.3)].

10 OVERDOSAGE

An excess of insulin relative to food intake, energy expenditure, or both may lead to severe and sometimes prolonged and life-threatening hypoglycemia and hypokalemia [see Warnings and Precautions (5.3, 5.6)]. Mild episodes of hypoglycemia usually can be treated with oral glucose. Lowering the insulin dosage, and adjustments in meal patterns, or exercise may be needed. More severe episodes with coma, seizure, or neurologic impairment may be treated with a glucagon product for emergency use or concentrated intravenous glucose. After apparent clinical recovery from hypoglycemia, continued observation and additional carbohydrate intake may be necessary to avoid recurrence of hypoglycemia. Hypokalemia must be corrected appropriately.

11 DESCRIPTION

Insulin detemir is a long-acting recombinant human insulin analog produced by a process that includes expression of recombinant DNA in Saccharomyces cerevisiae followed by chemical modification.

Insulin detemir differs from human insulin in that the amino acid threonine in position B30 has been omitted, and a C14 fatty acid chain has been attached to the amino acid B29. Insulin detemir has a molecular formula of C267H402O76N64S6 and a molecular weight of 5.917 kDa. It has the following structure:

Figure 1: Structural Formula of Insulin Detemir

LEVEMIR (insulin detemir) injection is a clear, colorless, aqueous, neutral sterile solution for subcutaneous use. Each milliliter of LEVEMIR contains 100 units insulin detemir, dibasic sodium phosphate (0.71 mg), glycerin (16 mg), metacresol (2.06 mg), phenol (1.8 mg), sodium chloride (1.17 mg), zinc (65.4 mcg), and Water for Injection, USP. Hydrochloric acid and/or sodium hydroxide may be added to adjust pH. LEVEMIR has a pH of approximately 7.4.

12 CLINICAL PHARMACOLOGY

12.1 Mechanism of Action

The primary activity of insulin, including LEVEMIR, is regulation of glucose metabolism. Insulins and its analogs lower blood glucose by stimulating peripheral glucose uptake, especially by skeletal muscle and fat, and by inhibiting hepatic glucose production. Insulin also inhibits lipolysis and proteolysis, and enhances protein synthesis.

12.2 Pharmacodynamics

Insulin detemir is a soluble, long-acting basal human insulin analog with up to a 24-hour duration of action. The pharmacodynamic profile of LEVEMIR is relatively constant with no pronounced peak.

The duration of action of LEVEMIR is mediated by slowed systemic absorption of insulin detemir molecules from the injection site due to self-association of the drug molecules. In addition, the distribution of insulin detemir to peripheral target tissues is slowed because of binding to albumin.

Figure 2 shows results from a study in patients with type 1 diabetes conducted for a maximum of 24 hours after the subcutaneous injection of LEVEMIR. The mean time between injection and the end of pharmacological effect for insulin detemir ranged from 7.6 hours to >24 hours (24 hours was the end of the observation period).

Figure 2: Glucose Lowering Effect in Patients with Type 1 Diabetes in a 24-hour Glucose Clamp Study

For doses in the interval of 0.2 to 0.4 units/kg, insulin detemir exerts more than 50% of its maximum effect from 3 to 4 hours up to approximately 14 hours after dose administration.

Figure 3 shows glucose infusion rate results from a 16-hour glucose clamp study in patients with type 2 diabetes. The clamp study was terminated at 16 hours according to protocol.

Figure 3: Glucose Lowering Effect in Patients with Type 2 Diabetes in a 16-hour Glucose Clamp Study

12.3 Pharmacokinetics

Absorption

After subcutaneous injection of LEVEMIR in healthy subjects and in patients with diabetes, insulin detemir serum concentrations had a relatively constant concentration/time profile over 24 hours with the maximum serum concentration (Cmax) reached between 6-8 hours post-dose. Insulin detemir was more slowly absorbed after subcutaneous administration to the thigh where AUC0-5h was 30-40% lower and AUC0-inf was 10% lower than the corresponding AUCs with subcutaneous injections to the deltoid and abdominal regions.

The absolute bioavailability of insulin detemir is approximately 60%.

Distribution

Insulin detemir has an apparent volume of distribution of approximately 0.1 L/kg. More than 98% of insulin detemir in the bloodstream is bound to albumin. The results of in vitro and in vivo protein binding studies demonstrate that there is no clinically relevant interaction between insulin detemir and fatty acids or other protein-bound drugs.

Elimination

After subcutaneous administration in patients with type 1 diabetes, insulin detemir has a terminal half-life of 5 to 7 hours depending on dose.

Specific Populations

Pediatric Patients

The pharmacokinetic properties of LEVEMIR were studied in pediatric patients 6-12 years, 13-17 years, and adults with type 1 diabetes. In pediatric patients 6-12 years, the insulin detemir plasma area under the curve (AUC) and Cmax were increased by 10% and 24%, respectively, as compared to adults. There was no difference in pharmacokinetics between pediatric patients 13-17 years and adults.

Geriatrics

In a clinical trial studying differences in pharmacokinetics of a single subcutaneous dose of LEVEMIR in young (20 to 35 years) versus elderly (≥68 years) healthy subjects, the insulin detemir AUC was up to 35% higher among the elderly subjects due to reduced clearance [see Use in Specific Populations (8.5)].

Gender

No clinically relevant differences in pharmacokinetic parameters of LEVEMIR are observed between males and females.

Race

In two clinical pharmacology studies conducted in healthy Japanese and Caucasian subjects, there were no clinically relevant differences seen in pharmacokinetic parameters. The pharmacokinetics and pharmacodynamics of LEVEMIR were studied in a clamp study comparing patients with type 2 diabetes of Caucasian, African-American, and Latino origin. Dose-response relationships for LEVEMIR were comparable in these three populations.

Renal impairment

A single subcutaneous dose of 0.2 units/kg of LEVEMIR was administered to healthy subjects and those with varying degrees of renal impairment (mild, moderate, severe, and hemodialysis-dependent). In this study, there were no differences in the pharmacokinetics of LEVEMIR between healthy subjects and those with renal impairment [see Use in Specific Populations (8.6)].

Hepatic impairment

A single subcutaneous dose of 0.2 units/kg of LEVEMIR was administered to healthy subjects and those with varying degrees of hepatic impairment (mild, moderate and severe). LEVEMIR exposure as estimated by AUC decreased with increasing degrees of hepatic impairment with a corresponding increase in apparent clearance [see Use in Specific Populations (8.7)].

Smoking

The effect of smoking on the pharmacokinetics and pharmacodynamics of LEVEMIR has not been studied.

Liraglutide

No pharmacokinetic interaction was observed between liraglutide and LEVEMIR when separate subcutaneous injections of LEVEMIR 0.5 units/kg (single-dose) and liraglutide 1.8 mg (steady state) were administered in patients with type 2 diabetes.

13 NONCLINICAL TOXICOLOGY

13.1 Carcinogenesis, Mutagenesis, Impairment of Fertility

Standard 2-year carcinogenicity studies in animals have not been performed. Insulin detemir tested negative for genotoxic potential in the in vitro reverse mutation study in bacteria, human peripheral blood lymphocyte chromosome aberration test, and the in vivo mouse micronucleus test.

In a fertility and embryonic development study, insulin detemir was administered to female rats before mating, during mating, and throughout pregnancy at doses up to 300 nmol/kg/day (3 times a human dose of 0.5 units/kg/day, based on plasma AUC ratio). There were no effects on fertility in the rat.

14 CLINICAL STUDIES

The efficacy and safety of LEVEMIR given once-daily at bedtime or twice-daily (before breakfast and at bedtime, before breakfast and with the evening meal, or at 12-hour intervals) was compared to that of once-daily or twice-daily NPH insulin in open-label, randomized, parallel trials of 1155 adults with type 1 diabetes mellitus, 347 pediatric patients with type 1 diabetes mellitus, and 869 adults with type 2 diabetes mellitus. The efficacy and safety of LEVEMIR given twice-daily was compared to once-daily insulin glargine in an open-label, randomized, parallel trial of 320 patients with type 1 diabetes. The evening LEVEMIR dose was titrated in all trials according to pre-defined targets for fasting blood glucose. The pre-dinner blood glucose was used to titrate the morning LEVEMIR dose in those trials that also administered LEVEMIR in the morning. In general, the reduction in HbA1c with LEVEMIR was similar to that with NPH insulin or insulin glargine.

14.1 Clinical Studies in Adult Patients with Type 1 Diabetes

In a 16-week open-label clinical trial (Study A, n=409), adults with type 1 diabetes were randomized to treatment with either LEVEMIR at 12-hour intervals, LEVEMIR administered in the morning and bedtime or NPH insulin administered in the morning and bedtime. Insulin aspart was also administered before each meal. At 16 weeks of treatment, the combined LEVEMIR-treated patients had similar HbA1c and fasting plasma glucose (FPG) reductions compared to the NPH-treated patients (Table 7). Differences in timing of LEVEMIR administration had no effect on HbA1c, fasting plasma glucose (FPG), or body weight.

In a 26-week, open-label clinical trial (Study B, n=320), adults with type 1 diabetes were randomized to twice-daily LEVEMIR (administered in the morning and bedtime) or once-daily insulin glargine (administered at bedtime). Insulin aspart was administered before each meal. LEVEMIR-treated patients had a decrease in HbA1c similar to that of insulin glargine-treated patients.

In a 24-week, open-label clinical trial (Study C, n=749), adults with type 1 diabetes were randomized to once-daily LEVEMIR or once-daily NPH insulin, both administered at bedtime and in combination with regular human insulin before each meal. LEVEMIR and NPH insulin had a similar effect on HbA1c.

Table 7: Type 1 Diabetes Mellitus – Adult
 | Study A |  | Study B |  | Study C
Treatment duration | 16 weeks |  | 26 weeks |  | 24 weeks
Treatment in combination with | NovoLog; (insulin aspart) |  | NovoLog; (insulin aspart) |  | Human Soluble Insulin; (regular insulin)
 | Twice-daily; LEVEMIR | Twice-daily; NPH | Twice-daily LEVEMIR | Once-daily insulin glargine | Once-daily LEVEMIR | Once-daily NPH
Number of patients treated | 276 | 133 | 161 | 159 | 492 | 257
HbA1c (%)
Baseline HbA1c | 8.6 | 8.5 | 8.9 | 8.8 | 8.4 | 8.3
Adj. mean change from; baseline | -0.8* | -0.7* | -0.6** | -0.5** | -0.1* | 0.0*
LEVEMIR – NPH; 95% CI for Treatment; difference | -0.2; (-0.3, -0.0) |  | -0.0; (-0.2, 0.2) |  | -0.1; (-0.3, 0.0)
Fasting blood glucose (mg/dL)
Baseline mean | 209 | 220 | 153 | 150 | 213 | 206
Adj. mean change from; baseline | -44* | -9* | -38** | -41** | -30* | -9*

*From an ANCOVA model adjusted for baseline value and country.

**From an ANCOVA model adjusted for baseline value and study site.

14.2 Clinical Studies in Pediatric Patients with Type 1 Diabetes

Two open-label, randomized, controlled clinical trials have been conducted in pediatric patients with type 1 diabetes. One trial (Study D) was 26 weeks in duration and enrolled patients 6 to 17 years of age. The other trial (Study I) was 52 weeks in duration and enrolled patients 2 to 16 years of age. In both trials, LEVEMIR and NPH insulin were administered once- or twice-daily. Bolus insulin aspart was administered before each meal. In the 26-week trial, LEVEMIR-treated patients had a mean decrease in HbA1c similar to that of NPH insulin (Table 8). In the 52-week trial, the randomization was stratified by age (2-5 years, n=82, and 6-16 years, n=265) and the mean HbA1c increased in both treatment arms, with similar findings in the 2-5 year-old age group (n=80) and the 6-16 year-old age group (n=258) (Table 8).

Table 8: Type 1 Diabetes Mellitus – Pediatric
 | Study D |  | Study I
Treatment duration | 26 weeks |  | 52 weeks
Treatment in combination with | NovoLog; (insulin aspart) |  | NovoLog; (insulin aspart)
 | Once- or Twice Daily LEVEMIR | Once- or Twice Daily NPH | Once- or Twice Daily LEVEMIR | Once- or Twice Daily NPH
Number of subjects treated | 232 | 115 | 177 | 170
HbA1c (%)
Baseline HbA1c | 8.8 | 8.8 | 8.4 | 8.4
Adj. mean change from baseline | -0.7* | -0.8* | 0.3** | 0.2**
LEVEMIR – NPH; 95% CI for Treatment; difference | 0.1; -0.1; 0.3 |  | 0.1; -0.1; 0.4
Fasting blood glucose (mg/dL)
Baseline mean | 181 | 181 | 135 | 141
Adj. mean change from baseline | -39 | -21 | -10** | 0**

*From an ANCOVA model adjusted for baseline value, geographical region, gender and age (covariate).

**From an ANCOVA model adjusted for baseline value, country, pubertal status at baseline and age (stratification factor).

14.3 Clinical Studies in Adult Patients with Type 2 Diabetes

In a 24-week, open-label, randomized, clinical trial (Study E, n=476), LEVEMIR administered twice-daily (before breakfast and evening) was compared to NPH insulin administered twice-daily (before breakfast and evening) as part of a regimen of stable combination therapy with one or two of the following oral antidiabetic medications: metformin, an insulin secretagogue, or an alpha–glucosidase inhibitor. All patients were insulin-naïve at the time of randomization. LEVEMIR and NPH insulin similarly lowered HbA1c from baseline (Table 9).

In a 22-week, open-label, randomized, clinical trial (Study F, n=395) in adults with type 2 diabetes, LEVEMIR and NPH insulin were given once- or twice-daily as part of a basal-bolus regimen with insulin aspart. As measured by HbA1c or FPG, LEVEMIR had efficacy similar to that of NPH insulin.

Table 9: Type 2 Diabetes Mellitus – Adult

 | Study E |  | Study F
Treatment duration | 24 weeks |  | 22 weeks
Treatment in combination with | oral agents |  | insulin aspart
 | Twice-daily; LEVEMIR | Twice-daily; NPH | Once- or Twice Daily LEVEMIR | Once- or Twice Daily; NPH
Number of subjects treated | 237 | 239 | 195 | 200
HbA1c (%)
Baseline HbA1c | 8.6 | 8.5 | 8.2 | 8.1
Adj. mean change from baseline | -2.0* | -2.1* | -0.6** | -0.6**
LEVEMIR – NPH; 95% CI for Treatment difference | 0.1; (-0.0, 0.3) |  | -0.1; (-0.2, 0.1)
Fasting blood glucose^1 (mg/dL)
Baseline mean | 179 | 173 | - | -
Adj. mean change from baseline | -69* | -74* | - | -

^1Study F - Fasting blood glucose data not collected

*From an ANCOVA model adjusted for baseline value, country and oral antidiabetic treatment category.

**From an ANCOVA model adjusted for baseline value and country.

Combination Therapy with Metformin and Liraglutide

This 26-week open-label trial enrolled 988 patients with inadequate glycemic control (HbA1c 7-10%) on metformin (≥1500 mg/day) alone or inadequate glycemic control (HbA1c 7-8.5%) on metformin (≥1500 mg/day) and a sulfonylurea. Patients who were on metformin and a sulfonylurea discontinued the sulfonylurea then all patients entered a 12-week run-in period during which they received add-on therapy with liraglutide titrated to 1.8 mg once-daily. At the end of the run-in period, 498 patients (50%) achieved HbA1c <7% with liraglutide 1.8 mg and metformin and continued treatment in a non-randomized, observational arm. Another 167 patients (17%) withdrew from the trial during the run-in period with approximately one-half of these patients doing so because of gastrointestinal adverse reactions. The remaining 323 patients with HbA1c ≥7% (33% of those who entered the run-in period) were randomized to 26 weeks of once-daily LEVEMIR administered in the evening as add-on therapy (n=162) or to continued, unchanged treatment with liraglutide 1.8 mg and metformin (n=161). The starting dose of LEVEMIR was 10 units/day and the mean dose at the end of the 26-week randomized period was 39 units/day. During the 26-week randomized treatment period, the percentage of patients who discontinued due to ineffective therapy was 11.2% in the group randomized to continued treatment with liraglutide 1.8 mg and metformin and 1.2% in the group randomized to add-on therapy with LEVEMIR.

Treatment with LEVEMIR as add-on to liraglutide 1.8 mg + metformin resulted in statistically significant reductions in HbA1c and FPG compared to continued, unchanged treatment with liraglutide 1.8 mg + metformin alone (Table 10). From a mean baseline body weight of 96 kg after randomization, there was a mean reduction of 0.3 kg in the patients who received LEVEMIR add-on therapy compared to a mean reduction of 1.1 kg in the patients who continued on unchanged treatment with liraglutide 1.8 mg + metformin alone.

Table 10: Results of a 26-week Open-label Trial of LEVEMIR as Add-on to Liraglutide + Metformin Compared to Continued Treatment with Liraglutide + Metformin Alone in Patients Not Achieving HbA1c <7% After 12 Weeks of Metformin and Liraglutide

 | Study H
 | LEVEMIR + Liraglutide +Metformin | Liraglutide+; Metformin
Intent-to-Treat Population (N)a | 162 | 157
HbA1c (%) (Mean)
Baseline (week 0) | 7.6 | 7.6
Adjusted mean change from baseline | -0.5* | 0*
Difference from liraglutide + metformin arm; (LS mean)b; 95% Confidence Interval | -0.5***; (-0.7, -0.4)
Percentage of patients achieving A1c <7% | 43** | 17**
Fasting Plasma Glucose (mg/dL) (Mean)
Baseline (week 0) | 166 | 159
Adjusted mean change from baseline | -38* | -7*
Difference from liraglutide + metformin arm; (LS mean)b; 95% Confidence Interval | -31***; (-39, -23)

aIntent-to-treat population using last observation on study

bLeast squares mean adjusted for baseline value

*From an ANCOVA model adjusted for baseline value, country and previous oral antidiabetic treatment category.

**From a logistic regression model adjusted for baseline HbA1c.

***p-value <0.0001

16 HOW SUPPLIED/STORAGE AND HANDLING

Product: 50090-1276

NDC: 50090-1276-0 10 mL in a VIAL, GLASS / 1 in a CARTON

Product: 50090-1475

17 PATIENT COUNSELING INFORMATION

See FDA-Approved Patient Labeling (Patient Information and Instructions for Use). There are separate Instructions for Use for the Vials and LEVEMIR FlexPen Prefilled Pen.

Never Share a LEVEMIR FlexPen or Insulin Syringe Between Patients

Advise patients that they must never share a LEVEMIR FlexPen with another person, even if the needle is changed. Advise patients using LEVEMIR vials not to share needles or insulin syringes with another person. Sharing poses a risk for transmission of blood-borne pathogens [see Warnings and Precautions (5.1)].

Hyperglycemia or Hypoglycemia

Inform patients that hypoglycemia is the most common adverse reaction with insulin. Inform patients of the symptoms of hypoglycemia (e.g., impaired ability to concentrate and react). This may present a risk in situations where these abilities are especially important, such as driving or operating other machinery. Advise patients who have frequent hypoglycemia or reduced or absent warning signs of hypoglycemia to use caution when driving or operating machinery [see Warnings and Precautions (5.3)].

Advise patients that changes in insulin regimen can predispose to hyperglycemia or hypoglycemia and that changes in insulin regimen should be made under close medical supervision [see Warnings and Precautions (5.2)].

Hypersensitivity Reactions

Advise patients that hypersensitivity reactions have occurred with LEVEMIR. Inform patients on the symptoms of hypersensitivity reactions [see Warnings and Precautions (5.5)].

Hypoglycemia Due to Medication Errors

Instruct patients to always check the insulin label before each injection to avoid mix-ups between insulin products [see Warnings and Precautions (5.4)].

Novo Nordisk®, Levemir®, NovoLog®, FlexPen®, and NovoFine® are registered trademarks of Novo Nordisk A/S.

Patent Information: https://www.novonordisk-us.com/products/product-patents.html

© 2005-2022 Novo Nordisk

Manufactured by:

Novo Nordisk Inc.

800 Scudders Mill Road

Plainsboro, NJ 08536

U.S. License Number 1261

For information about LEVEMIR contact:

Novo Nordisk Inc.

800 Scudders Mill Road

Plainsboro, New Jersey 08536

1-800-727-6500

www.novonordisk-us.com

Patient Information

LEVEMIR® (LEV–uh-mere)

(insulin detemir)

injection, for subcutaneous use

Do not share your LEVEMIR FlexPen with other people, even if the needle has been changed. Do not share needles or syringes with another person. You may give other people a serious infection or get a serious infection from them.

What is LEVEMIR?

- LEVEMIR is a man-made insulin that is used to control high blood sugar in adults and children with diabetes mellitus.
- LEVEMIR is not for people with diabetic ketoacidosis (increased ketones in the blood or urine).

Who should not take LEVEMIR?

Do not take LEVEMIR if you:

- are having an episode of low blood sugar (hypoglycemia).
- have an allergy to LEVEMIR or any of the ingredients in LEVEMIR. See the end of this Patient Information leaflet for a complete list of ingredients in LEVEMIR.

Before taking LEVEMIR, tell your healthcare provider about all your medical conditions including, if you:

- take any other medicines, especially medicines commonly called TZDs (thiazolidinediones).
- are pregnant, planning to become pregnant, or are breastfeeding.

Tell your healthcare provider all the medicines you take, including prescription and over-the-counter medicines, vitamins, or herbal supplements. Before you start taking LEVEMIR, talk to your healthcare provider about low blood sugar and how to manage it.

How should I take LEVEMIR?

- Read the Instructions for Use that comes with your LEVEMIR.
- Take LEVEMIR exactly as your healthcare provider tells you to.
- Know the type and strength of insulin you take. Do not change the type of insulin you take unless your healthcare provider tells you to. The amount of insulin and the best time for you to take your insulin may need to change if you take different types of insulin.
- Check your blood sugar levels. Ask your healthcare provider what your blood sugars should be and when you should check your blood sugar levels.
- Do not reuse or share your needles or syringes with other people. You may give other people a serious infection or get a serious infection from them.
- LEVEMIR is injected under the skin (subcutaneously) of your upper legs (thighs), upper arms, or stomach area (abdomen).
- Do not inject LEVEMIR into a vein or muscle.
- Change (rotate) your injection sites within the area you choose with each dose to reduce your risk of getting lipodystrophy (pits in skin or thickened skin) and localized cutaneous amyloidosis (skin with lumps) at the injection sites.
- Do not use the exact same spot for each injection.
- Do not inject where the skin has pits, is thickened, or has lumps.
- Do not inject where the skin is tender, bruised, scaly or hard, or into scars or damaged skin.

What should I avoid while taking LEVEMIR?

While taking LEVEMIR do not:

- Drive or operate heavy machinery, until you know how LEVEMIR affects you.
- Drink alcohol or use prescription or over-the-counter medicines that contain alcohol.

What are the possible side effects of LEVEMIR?

LEVEMIR may cause serious side effects that can lead to death, including:

- low blood sugar (hypoglycemia). Low blood sugar can be a serious, but common side effect of LEVEMIR. Signs and symptoms that may indicate low blood sugar include:
- dizziness or light-headedness
- sweating
- confusion
- headache
- blurred vision
- slurred speech
- shakiness
- fast heartbeat
- anxiety, irritability, or mood changes
- hunger
- severe allergic reactions. Severe allergic reactions are a potential side effect of LEVEMIR. Get emergency medical help if you have:
- trouble breathing
- shortness of breath
- fast heartbeat
- swelling
- swelling of your face, tongue, or throat
- sweating
- extreme drowsiness
- dizziness
- confusion
- low potassium in your blood (hypokalemia).
- heart failure. Taking certain diabetes pills called TZDs (thiazolidinediones) with LEVEMIR may cause heart failure in some people. This can happen even if you have never had heart failure or heart problems before. If you already have heart failure, it may get worse while you take TZDs with LEVEMIR. Tell your healthcare provider if you have any new or worse symptoms of heart failure including:
- shortness of breath
- swelling of ankles or feet
- sudden weight gain

Treatment with TZDs and LEVEMIR may need to be changed or stopped by your healthcare provider if you have new or worse heart failure.

Other common side effects of LEVEMIR include:

- injection site reactions
- skin thickening or pits at the injection site (lipodystrophy)
- weight gain
- swelling of your hands and feet
- rash
- itching

Your insulin dose may need to change because of:

- change in level of physical activity or exercise
- weight gain or loss
- increased stress
- illness
- change in diet

Tell your healthcare provider if you have any side effect that bothers you or that does not go away.

These are not all the possible side effects of LEVEMIR. Call your doctor for medical advice about side effects. You may report side effects to FDA at 1-800-FDA-1088.

General information about the safe and effective use of LEVEMIR.

Medicines are sometimes prescribed for purposes other than those listed in a Patient Information Leaflet. Do not use LEVEMIR for a condition for which it was not prescribed. Do not give LEVEMIR to other people, even if they have the same symptoms that you have. It may harm them. You can ask your pharmacist or healthcare provider for information about LEVEMIR that is written for health professionals.

What are the ingredients in LEVEMIR?

Active Ingredient: insulin detemir

Inactive Ingredients: dibasic sodium phosphate, glycerin, metacresol, phenol, sodium chloride, zinc and Water for Injection, USP. Hydrochloric acid or sodium hydroxide may be added.

Manufactured by:

Novo Nordisk Inc.

800 Scudders Mill Road

Plainsboro, NJ 08536

U.S. License Number 1261

For more information, go to www.novonordisk-us.com or call 1-800-727-6500.

This Patient Information has been approved by the U.S. Food and Drug Administration.

Revised: 12/2022

INSTRUCTIONS FOR USE

LEVEMIR® (LEV-uh-mere)

injection, for subcutaneous use

10 mL multiple-dose vial

Please read the following Instructions for use carefully before using your LEVEMIR® vial and each time you get a refill. You should read the instructions in this manual even if you have used an insulin vial before.

How should I use the LEVEMIR vial?

Using the vial:

1. Check to make sure that you have the correct type of insulin. This is especially important if you use different types of insulin.

2. Look at the vial and the insulin. The LEVEMIR insulin should be clear and colorless. The tamper-resistant cap should be in place before the first use. If the cap has been removed before your first use of the vial, or if the insulin is cloudy or colored, do not use the insulin and return it to your pharmacy.

3. Wash your hands with soap and water.

4. If you are using a new vial, pull off the tamper-resistant cap.

Before each use, wipe the rubber stopper with an alcohol wipe.

5. Do not roll or shake the vial. Shaking the vial right before the dose is drawn into the syringe may cause bubbles or foam. This can cause you to draw up the wrong dose of insulin. The insulin should be used only if it is clear and colorless.

6. Pull back the plunger on your syringe until the black tip reaches the marking for the number of units you will inject.

7. Push the needle through the rubber stopper into the vial.

8. Push the plunger all the way in. This inserts air into the vial.

9. Turn the vial and syringe upside down and slowly pull the plunger back to a few units beyond the correct dose that you need.

10. If there are air bubbles, tap the syringe gently with your finger to raise the air bubbles to the top of the needle. Then slowly push the plunger to the correct unit marking for your dose.

11. Check to make sure you have the right dose of LEVEMIR in the syringe.

12. Pull the syringe out of the vial.

13. Inject your LEVEMIR right away as instructed by your healthcare provider. LEVEMIR can be injected under the skin (subcutaneously) of your stomach area (abdomen), upper legs (thighs) or upper arms. For each injection, change (rotate) your injection site within the area of skin that you use to reduce your risk of getting lipodystrophy (pits in skin or thickened skin) and localized cutaneous amyloidosis (skin with lumps) at the injection sites. Do not use the same injection site for each injection. Do not inject where the skin has pits, is thickened, or has lumps. Do not inject where the skin is tender, bruised, scaly or hard, or into scars or damaged skin.

How should I inject LEVEMIR with a syringe?

If you clean your injection site with an alcohol swab, let the injection site dry before you inject. Talk with your healthcare provider about how to rotate injection sites and how to give an injection.

1. Pinch your skin between two fingers, push the needle into the skinfold, using a dart-like motion and push the plunger to inject the insulin under your skin. The needle will be straight in.

2. Keep the needle under your skin for at least 6 seconds to make sure you have injected all the insulin. After you pull the needle from your skin you may see a drop of LEVEMIR at the needle tip. This is normal and has no effect on the dose you just received.

3. If blood appears after you pull the needle from your skin, press the injection site lightly with an alcohol swab. Do not rub the area.

4. After each injection, remove the needle without recapping and dispose of it in a puncture-resistant container. Used vials, syringes, needles, and lancets should be placed in sharps containers (such as red biohazard containers), hard plastic containers (such as detergent bottles), or metal containers (such as an empty coffee can). Such containers should be sealed and disposed of properly.

How should I store LEVEMIR?

- Do not freeze LEVEMIR. Do not use LEVEMIR if it has been frozen.
- Keep LEVEMIR away from heat or light.
- All unopened vials:
  - Store unopened LEVEMIR vials in the refrigerator at 36°F to 46°F (2°C to 8°C).
  - Unopened vials may be used until the expiration date printed on the label, if they have been stored in the refrigerator.
  - Unopened vials should be thrown away after 42 days, if they are stored at room temperature up to 86°F (30°C).
- After vials have been opened:
- Opened LEVEMIR vials can be stored in the refrigerator at 36°F to 46°F (2°C to 8°C) or at room temperature up to 86°F (30°C).
- Throw away all opened LEVEMIR vials after 42 days, even if they still have insulin left in them.

Revised: 07/2022

Novo Nordisk® and LEVEMIR® are registered trademarks of Novo Nordisk A/S.

PATENT Information: https://www.novonordisk-us.com/products/product-patents.html

© 2005-2022 Novo Nordisk

Manufactured by:

Novo Nordisk Inc.

800 Scudders Mill Road

Plainsboro, NJ 08536

U.S. License Number 1261

INSTRUCTIONS FOR USE

Levemir® (LEV–uh-mere)

(insulin detemir)

injection, for subcutaneous use

FlexTouch® Pen

Please read the following instructions carefully before using your Levemir FlexTouch Pen.

- Do not share your Levemir FlexTouch Pen with other people, even if the needle has been changed. You may give other people a serious infection, or get a serious infection from them.
- Levemir FlexTouch Pen (“Pen”) is a prefilled disposable, single-patient-use insulin pen containing 300 units insulin detemir. You can inject from 1 to 80 units in a single injection.
- People who are blind or have vision problems should not use this Pen without help from a person trained to use the Pen.

Supplies you will need to give your Levemir injection:

- Levemir FlexTouch Pen
- a new NovoFine, NovoFine Plus or NovoTwist needle
- alcohol swab
- 1 sharps container for throwing away used Pens and needles. See “Disposing of used Levemir FlexTouch Pens and needles” at the end of these instructions.

Preparing your Levemir FlexTouch Pen:

- Wash your hands with soap and water.
- Before you start to prepare your injection, check the Levemir FlexTouch Pen label to make sure you are taking the right type of insulin. This is especially important if you take more than 1 type of insulin.
- Levemir should look clear and colorless. Do not use Levemir if it is thick, cloudy, or is colored.
- Do not use Levemir past the expiration date printed on the label or 42 days after you start using the Pen.
- Always use a new needle for each injection to help ensure sterility and prevent blocked needles. Do not reuse or share your needles with other people. You may give other people a serious infection, or get a serious infection from them.

Step 1:

- Pull Pen cap straight off (See Figure B).

Step 2:

- Check the liquid in the Pen (See Figure C). Levemir should look clear and colorless. Do not use it if it looks cloudy or colored.

Step 3:

- Select a new needle.
- Pull off the paper tab from the outer needle cap (See Figure D).

Step 4:

- Push the capped needle straight onto the Pen and twist the needle on until it is tight (See Figure E).

Step 5:

- Pull off the outer needle cap. Do not throw it away (See Figure F).

Step 6:

- Pull off the inner needle cap and throw it away (See Figure G).

Priming your Levemir FlexTouch Pen:

Step 7:

- Turn the dose selector to select 2 units (See Figure H).

Step 8:

- Hold the Pen with the needle pointing up. Tap the top of the Pen gently a few times to let any air bubbles rise to the top (See Figure I).

Step 9:

- Hold the Pen with the needle pointing up. Press and hold in the dose button until the dose counter shows “0”. The “0” must line up with the dose pointer.
- A drop of insulin should be seen at the needle tip (See Figure J).
  - If you do not see a drop of insulin, repeat steps 7 to 9, no more than 6 times.
  - If you still do not see a drop of insulin, change the needle and repeat steps 7 to 9.

Selecting your dose:

Step 10:

- Turn the dose selector to select the number of units you need to inject. The dose pointer should line up with your dose (See Figure K).
  - If you select the wrong dose, you can turn the dose selector forwards or backwards to the correct dose.
  - The even numbers are printed on the dial.
  - The odd numbers are shown as lines.

- The Levemir FlexTouch Pen insulin scale will show you how much insulin is left in your Pen (See Figure L).
- To see how much insulin is left in your Levemir FlexTouch Pen:
- Turn the dose selector until it stops. The dose counter will line up with the number of units of insulin that is left in your Pen. If the dose counter shows 80, there are at least 80 units left in your Pen.
- If the dose counter shows less than 80, the number shown in the dose counter is the number of units left in your Pen.

Giving your injection:

- Inject your Levemir exactly as your healthcare provider has shown you. Your healthcare provider should tell you if you need to pinch the skin before injecting.
- Levemir can be injected under the skin (subcutaneously) of your stomach area (abdomen), upper legs (thighs) or upper arms.
- For each injection, change (rotate) your injection site within the area of skin that you use to reduce your risk of getting lipodystrophy (pits in skin or thickened skin) and localized cutaneous amyloidosis (skin with lumps) at the injection sites. Do not use the same injection site for each injection. Do not inject where the skin has pits, is thickened, or has lumps. Do not inject where the skin is tender, bruised, scaly or hard, or into scars or damaged skin.

Step 11:

- Choose your injection site (abdomen, thighs or upper arms) and wipe the skin with an alcohol swab. Let the injection site dry before you inject your dose (See Figure M).

Step 12:

- Insert the needle into your skin (See Figure N).
- Make sure you can see the dose counter. Do not cover it with your fingers; this can stop your injection.

Step 13:

- Press and hold down the dose button until the dose counter shows “0” (See Figure O).
- The “0” must line up with the dose pointer. You may then hear or feel a click.

- Keep the needle in your skin after the dose counter has returned to “0” and slowly count to 6 (See Figure P).
- When the dose counter returns to “0”, you will not get your full dose until 6 seconds later.
- If the needle is removed before you count to 6, you may see a stream of insulin coming from the needle tip.
- If you see a stream of insulin coming from the needle tip you will not get your full dose. If this happens you should check your blood sugar levels more often because you may need more insulin.

Step 14:

- Pull the needle out of your skin (See Figure Q).
- If you see blood after you take the needle out of your skin, press the injection site lightly with a piece of gauze or an alcohol swab. Do not rub the area.

Step 15:

- Carefully remove the needle from the Pen and throw it away (See Figure R).
  - Do not recap the needle. Recapping the needle can lead to needle stick injury.
- If you do not have a sharps container, carefully slip the needle into the outer needle cap (See Figure S). Safely remove the needle and throw it away as soon as you can.
  - Do not store the Pen with the needle attached. Storing without the needle attached helps prevent leaking, blocking of the needle, and air from entering the Pen.

Step 16:

- Replace the Pen cap by pushing it straight on (See Figure T).

After your injection:

- The used Levemir FlexTouch Pen may be thrown away in your household trash after you have removed the needle.
- You can put your used needles in a FDA-cleared sharps disposal container right away after use. Do not throw away (dispose of) loose needles in your household trash.
- If you do not have a FDA-cleared sharps disposal container, you may use a household container that is:
  - made of a heavy-duty plastic
  - can be closed with a tight-fitting, puncture-resistant lid, without sharps being able to come out
  - upright and stable during use
  - leak-resistant
  - properly labeled to warn of hazardous waste inside the container
- When your sharps disposal container is almost full, you will need to follow your community guidelines for the right way to dispose of your sharps disposal container. There may be state or local laws about how you should throw away used needles and syringes. Do not reuse or share your needles or syringes with other people. For more information about safe sharps disposal, and for specific information about sharps disposal in the state that you live in, go to the FDA’s website at: http://www.fda.gov/safesharpsdisposal.
- Do not dispose of your used sharps disposal container in your household trash unless your community guidelines permit this. Do not recycle your used sharps disposal container.

How should I store my Levemir FlexTouch Pen?

- Store unused Levemir FlexTouch Pens in the refrigerator at 36°F to 46°F (2°C to 8°C).
- Store the Pen you are currently using out of the refrigerator up to 86°F.
- Do not freeze Levemir. Do not use Levemir if it has been frozen.
- Keep Levemir away from heat or light.
- Unused Pens may be used until the expiration date printed on the label, if kept in the refrigerator.
- The Levemir FlexTouch Pen you are using should be thrown away after 42 days, even if it still has insulin left in it.

General Information about the safe and effective use of Levemir:

- Keep Levemir FlexTouch Pens and needles out of the reach of children.
- Always use a new needle for each injection.
- Do not share your Levemir FlexTouch Pen or needles with other people. You may give other people a serious infection, or get a serious infection from them.

This Instructions for Use has been approved by the U.S. Food and Drug Administration.

Manufactured by:
Novo Nordisk Inc.

800 Scudders Mill Road

Plainsboro, NJ 08536

U.S. License Number 1261

Revised: 07/2022

For more information go to

www.novotraining.com/levemirflextouch/us02

© 2005-2022 Novo Nordisk

Levemir®

FlexTouch®

Read before first use

Instructions For Use

LEVEMIR® (LEV–uh-mere) FlexPen®

(insulin detemir)

injection, for subcutaneous use

Please read the following instructions carefully before using your LEVEMIR FlexPen.

Do not share your LEVEMIR FlexPen with other people, even if the needle has been changed. You may give other people a serious infection or get a serious infection from them.

LEVEMIR FlexPen is a prefilled disposable, single-patient-use, insulin pen. You can select doses from 1 to 60 units in increments of 1 unit. LEVEMIR FlexPen is designed to be used with NovoFine or NovoFine Plus needles.

People who are blind or have vision problems should not use this Pen without help from a person trained to use the Pen.

Getting ready

Make sure you have the following items:

- LEVEMIR FlexPen
- NovoFine or NovoFine Plus disposable needles
- Alcohol swab
- Sharps disposal container (see After the Injection)

Preparing your LEVEMIR FlexPen

Wash your hands with soap and water. Before you start to prepare your injection, check the label to make sure that you are taking the right type of insulin. This is especially important if you take more than 1 type of insulin. LEVEMIR should look clear and colorless. Do not use LEVEMIR if it is thick, cloudy, or is colored.

A. Pull off the pen cap (see diagram A).

Wipe the rubber stopper with an alcohol swab.

B. Attaching the needle

Remove the protective tab from a new disposable needle.

Screw the needle tightly onto your FlexPen. It is important that the needle is put on straight (see diagram B).

Never place a disposable needle on your LEVEMIR FlexPen until you are ready to give your injection.

C. Pull off the big outer needle cap (see diagram C).

D. Pull off the inner needle cap and throw it away (dispose of it) (see diagram D).

Always use a new needle for each injection to make sure the needle is free of germs (sterile) and to prevent blocked needles. Do not reuse or share your needles with other people. You may give other people a serious infection or get a serious infection from them.

Be careful not to bend or damage the needle before use.

To reduce the risk of needle sticks, never put the inner needle cap back on the needle.

Giving the airshot before each injection

Before each injection, small amounts of air may collect in the cartridge during normal use. To avoid injecting air and to ensure proper dosing:

E. Turn the dose selector to select 2 units (see diagram E).

F. Hold your LEVEMIR FlexPen with the needle pointing up. Tap the cartridge gently with your finger a few times to make any air bubbles collect at the top of the cartridge (see diagram F).

G. Keep the needle pointing upwards, press the green push-button all the way in (see diagram G). The dose selector returns to 0.

A drop of insulin should appear at the needle tip. If not, change the needle and repeat the procedure no more than 6 times.

If you do not see a drop of insulin after 6 times, do not use the LEVEMIR FlexPen and contact Novo Nordisk at 1-800-727-6500.

A small air bubble may remain at the needle tip, but it will not be injected.

Selecting your dose

Check and make sure that the dose selector is set at 0.

H. Turn the dose selector to the number of units you need to inject. The pointer should line up with your dose.

The dose can be corrected either up or down by turning the dose selector in either direction until the correct dose lines up with the pointer (see diagram H). When turning the dose selector, be careful not to press the green push-button as insulin will come out.

You cannot select a dose larger than the number of units left in the cartridge.

You will hear a click for every single unit dialed. Do not set the dose by counting the number of clicks you hear because you may get an incorrect dose.

Do not use the cartridge scale printed on the cartridge to measure your dose of insulin.

Giving the injection

Give the injection exactly as shown to you by your healthcare provider. Your healthcare provider should tell you if you need to pinch the skin before injecting. Wipe the skin with an alcohol swab and let the area dry.

LEVEMIR can be injected under the skin (subcutaneously) of your stomach area (abdomen), upper legs (thighs), or upper arms.

Change (rotate) your injection sites within the area you choose for each dose to reduce your risk of getting lipodystrophy (pits in skin or thickened skin) and localized cutaneous amyloidosis (skin with lumps) at the injection sites. Do not use the same injection site for each injection. Do not inject where the skin has pits, is thickened, or has lumps. Do not inject where the skin is tender, bruised, scaly or hard, or into scars or damaged skin.

I. Insert the needle into your skin.

Inject the dose by pressing the green push-button all the way in until the 0 lines up with the pointer (see diagram I). Be careful only to push the green push-button when injecting.

Turning the dose selector will not inject the insulin.

J. Keep the needle in the skin for at least 6 seconds, and keep the green push-button pressed all the way in until the needle has been pulled out from the skin (see diagram J). This will make sure that the full dose has been given.

You may see a drop of insulin at the needle tip. This is normal and has no effect on the dose you just received. If blood appears after you take the needle out of your skin, press the injection site lightly with an alcohol swab. Do not rub the area.

After the injection

Do not recap the needle. Recapping can lead to a needle stick injury. Remove the needle from the LEVEMIR FlexPen after each injection and dispose of it. This helps to prevent infection, leakage of insulin, and will help to make sure you inject the right dose of insulin.

- If you do not have a sharps container, carefully slip the needle into the outer needle cap using 1 hand. Use your other hand to pinch the base of the big outer needle cap and unscrew the used needle from the Pen and throw it away as soon as you can.
- The used LEVEMIR FlexPen may be thrown away in your household trash after you have removed the needle.
- Put your used needles in an FDA-cleared sharps disposal container right away after use. Do not throw away (dispose of) loose needles in your household trash.
- If you do not have a FDA-cleared sharps disposal container, you may use a household container that is:
- made of a heavy-duty plastic,
- can be closed with a tight-fitting, puncture-resistant lid, without sharps being able to come out,
- upright and stable during use,
- leak-resistant, and
- properly labeled to warn of hazardous waste inside the container.
- When your sharps disposal container is almost full, you will need to follow your community guidelines for the right way to dispose of your sharps disposal container. There may be state or local laws about how you should throw away used needles and syringes. For more information about the safe sharps disposal, and for specific information about sharps disposal in the state that you live in, go to the FDA’s website at: http://www.fda.gov/safesharpsdisposal.

Do not dispose of your used sharps disposal container in your household trash unless your community guidelines permit this. Do not recycle your used sharps disposal container.

When there is not enough medicine left in your LEVEMIR FlexPen for your prescribed dose, the LEVEMIR FlexPen may be thrown away in your household trash after you have removed the needle.

The LEVEMIR FlexPen prevents the cartridge from being completely emptied. It is designed to deliver 300 units.

K. Put the pen cap on the LEVEMIR FlexPen and store the LEVEMIR FlexPen without the needle attached (see diagram K).

Storing without the needle attached helps prevent leaking, blocking of the needle, and air from entering the LEVEMIR FlexPen.

How should I store LEVEMIR FlexPen?

- Store the unused (unopened) LEVEMIR FlexPen in the refrigerator between 36°F to 46°F (2°C to 8°C).
- Store the LEVEMIR FlexPen you are currently using out of the refrigerator up to 86°F.
- Do not freeze the LEVEMIR FlexPen. Do not use the LEVEMIR FlexPen if it has been frozen.
- Keep the LEVEMIR FlexPen away from heat or light.
- Unused LEVEMIR FlexPens may be used until the expiration date printed on the label, if kept in the refrigerator.

The LEVEMIR FlexPen you are using should be thrown away after 42 days, even if it still has insulin left in it.

Keep your LEVEMIR FlexPen and needles out of the reach of children.

Maintenance

For the safe and proper use of your LEVEMIR FlexPen be sure to handle it with care. Avoid dropping your LEVEMIR FlexPen as it may damage it. If you are concerned that your LEVEMIR FlexPen is damaged, use a new one. You can clean the outside of your LEVEMIR FlexPen by wiping it with a damp cloth. Do not soak or wash your LEVEMIR FlexPen as it may damage it. Do not refill your LEVEMIR FlexPen.

Remove the needle from the LEVEMIR FlexPen after each injection. This helps to ensure sterility, prevent leakage of insulin, and will help to make sure you inject the right dose of insulin for future injections.

Be careful when handling used needles to avoid needle sticks and transfer of infectious diseases.

Use the LEVEMIR FlexPen exactly as your healthcare provider tells you to.

Do not share your LEVEMIR FlexPen or needles with other people. You may give other people a serious infection, or get a serious infection from them.

Always use a new needle for each injection.

Novo Nordisk is not responsible for harm due to using this insulin pen with products not recommended by Novo Nordisk.

As a precautionary measure, always carry a spare insulin delivery device in case your LEVEMIR FlexPen is lost or damaged.

Remember to keep the disposable LEVEMIR FlexPen with you. Do not leave it in a car or other location where it can get too hot or too cold.

© 2022 Novo Nordisk

This Instructions for Use has been approved by the U.S. Food and Drug Administration.

Manufactured by:

Novo Nordisk Inc.

800 Scudders Mill Road

Plainsboro, NJ 08536

U.S. License Number 1261

Revised: 12/2022